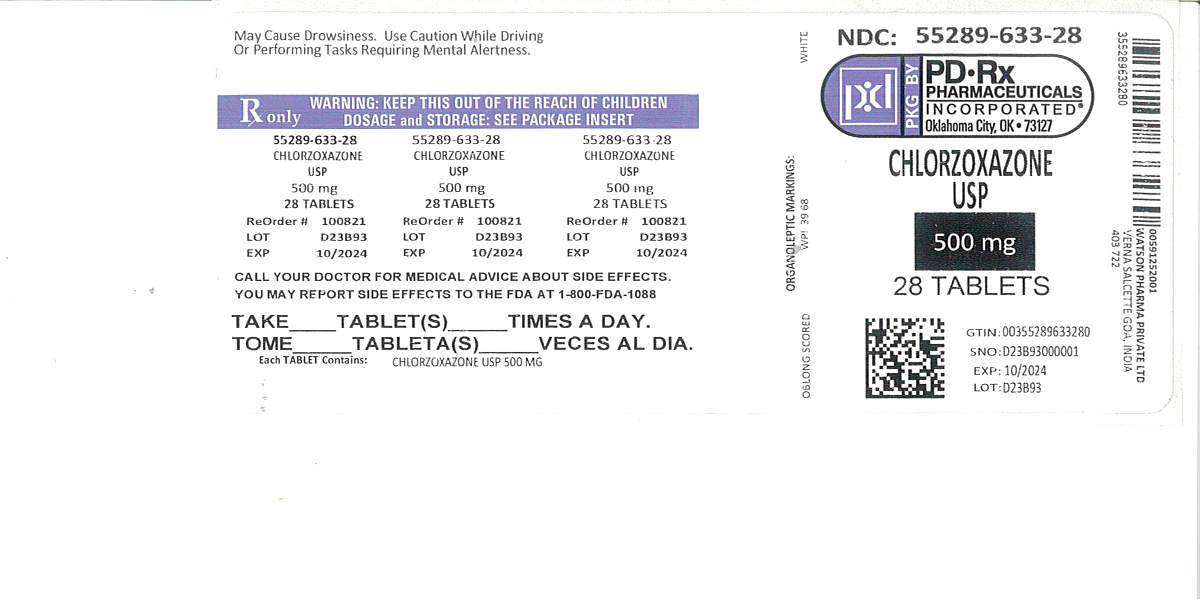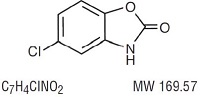 DRUG LABEL: Chlorzoxazone
NDC: 55289-633 | Form: TABLET
Manufacturer: PD-Rx Pharmaceuticals, Inc.
Category: prescription | Type: HUMAN PRESCRIPTION DRUG LABEL
Date: 20251020

ACTIVE INGREDIENTS: CHLORZOXAZONE 500 mg/1 1
INACTIVE INGREDIENTS: DOCUSATE SODIUM; LACTOSE MONOHYDRATE; MAGNESIUM STEARATE; CELLULOSE, MICROCRYSTALLINE; STARCH, CORN; SODIUM BENZOATE; SODIUM STARCH GLYCOLATE TYPE A POTATO

Chlorzoxazone Tablets, USP
Rx only

DESCRIPTION

Chlorzoxazone, USP is a centrally-acting skeletal muscle relaxant, available as tablets of 500 mg for oral administration. Its chemical name is 5-Chloro-2-benzoxazolinone, and its structural formula is:

Chlorzoxazone, USP is a white or practically white, practically odorless, crystalline powder. Chlorzoxazone, USP is slightly soluble in water; sparingly soluble in alcohol, in isopropyl alcohol, and in methanol; soluble in solutions of alkali hydroxides and ammonia.

Chlorzoxazone Tablets, USP contain the inactive ingredients docusate sodium, lactose monohydrate, magnesium stearate, microcrystalline cellullose, pregelatinized starch, sodium benzoate, and sodium starch glycolate.

CLINICAL PHARMACOLOGY

Chlorzoxazone is a centrally-acting agent for painful musculoskeletal conditions. Data available from animal experiments as well as human study indicate that chlorzoxazone acts primarily at the level of the spinal cord and subcortical areas of the brain where it inhibits multisynaptic reflex arcs involved in producing and maintaining skeletal muscle spasm of varied etiology. The clinical result is a reduction of the skeletal muscle spasm with relief of pain and increased mobility of the involved muscles. Blood levels of chlorzoxazone can be detected in people during the first 30 minutes and peak levels may be reached, in the majority of the subjects, in about 1 to 2 hours after oral administration of chlorzoxazone. Chlorzoxazone is rapidly metabolized and is excreted in the urine, primarily in a conjugated form as the glucuronide. Less than one percent of a dose of chlorzoxazone is excreted unchanged in the urine in 24 hours.

INDICATIONS

Chlorzoxazone is indicated as an adjunct to rest, physical therapy, and other measures for the relief of discomfort associated with acute, painful musculoskeletal conditions. The mode of action of this drug has not been clearly identified, but may be related to its sedative properties. Chlorzoxazone does not directly relax tense skeletal muscles in man.

CONTRAINDICATIONS

Chlorzoxazone is contraindicated in patients with known intolerance to the drug.

WARNINGS

Serious (including fatal) hepatocellular toxicity has been reported rarely in patients receiving chlorzoxazone. The mechanism is unknown but appears to be idiosyncratic and unpredictable. Factors predisposing patients to this rare event are not known. Patients should be instructed to report early signs and/or symptoms of hepatotoxicity such as fever, rash, anorexia, nausea, vomiting, fatigue, right upper quadrant pain, dark urine, or jaundice. Chlorzoxazone should be discontinued immediately and a physician consulted if any of these signs or symptoms develop. Chlorzoxazone use should also be discontinued if a patient develops abnormal liver enzymes (e.g., AST, ALT, alkaline phosphatase and bilirubin).

The concomitant use of alcohol or other central nervous system depressants may have an additive effect.

Usage in Pregnancy

The safe use of chlorzoxazone has not been established with respect to the possible adverse effects upon fetal development. Therefore, it should be used in women of childbearing potential only when, in the judgment of the physician, the potential benefits outweigh the possible risks.

PRECAUTIONS

Chlorzoxazone should be used with caution in patients with known allergies or with a history of allergic reactions to drugs. If a sensitivity reaction occurs such as urticaria, redness, or itching of the skin, the drug should be stopped.

If any symptoms suggestive of liver dysfunction are observed, the drug should be discontinued.

ADVERSE REACTIONS

Chlorzoxazone containing products are usually well tolerated. It is possible in rare instances that chlorzoxazone may have been associated with gastrointestinal bleeding. Drowsiness, dizziness, lightheadedness, malaise, or over-stimulation may be noted by an occasional patient. Rarely, allergic-type skin rashes, petechiae, or ecchymoses may develop during treatment. Angioneurotic edema or anaphylactic reactions are extremely rare. There is no evidence that the drug will cause renal damage. Rarely, a patient may note discoloration of the urine resulting from a phenolic metabolite of chlorzoxazone. This finding is of no known clinical significance.

To report SUSPECTED ADVERSE REACTIONS, contact Teva at 1-888-838-2872 or FDA at 1-800-FDA-1088 or www.fda.gov/medwatch.

OVERDOSAGE

Symptoms

Initially, gastrointestinal disturbances such as nausea, vomiting, or diarrhea together with drowsiness, dizziness, lightheadedness or headache may occur. Early in the course there may be malaise or sluggishness followed by marked loss of muscle tone, making voluntary movement impossible. The deep tendon reflexes may be decreased or absent. The sensorium remains intact, and there is no peripheral loss of sensation. Respiratory depression may occur with rapid, irregular respiration and intercostal and substernal retraction. The blood pressure is lowered, but shock has not been observed.

Treatment

Gastric lavage or induction of emesis should be carried out, followed by administration of activated charcoal. Thereafter, treatment is entirely supportive. If respirations are depressed, oxygen and artificial respiration should be employed and a patent airway assured by use of an oropharyngeal airway or endotracheal tube. Hypotension may be counteracted by use of dextran, plasma, concentrated albumin or a vasopressor agent such as norepinephrine. Cholinergic drugs or analeptic drugs are of no value and should not be used.

DOSAGE AND ADMINISTRATION

Usual Adult Dosage

One tablet three or four times daily. If adequate response is not obtained with this dose, it may be increased to one and one-half tablets (750 mg) three or four times daily. As improvement occurs dosage can usually be reduced.

HOW SUPPLIED

Chlorzoxazone Tablets USP, 500 mg are available as oblong, scored, white tablets debossed with "WPI" on one side and "39|68" on the other side and are packaged in bottles of:

(NDC 55289-633-10) Bottle of 10

(NDC 55289-633-20) Bottle of 20

(NDC 55289-633-24) Bottle of 24

(NDC 55289-633-28) Bottle of 28

(NDC 55289-633-30) Bottle of 30

(NDC 55289-633-40) Bottle of 40

Store at 20° to 25°C (68° to 77°F) [See USP Controlled Room Temperature].

Dispense contents with a child-resistant closure (as required) and in a tight container as defined in the USP/NF.

Keep this and all medications out of the reach of children.

PRINCIPAL DISPLAY PANEL

Chlorzoxazone Tablets, USP
500 mg
Rx only